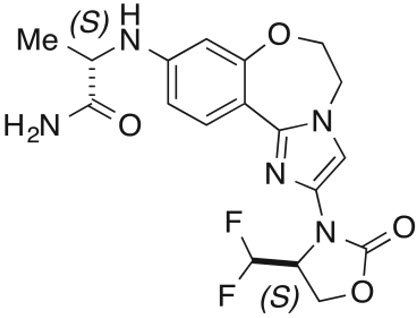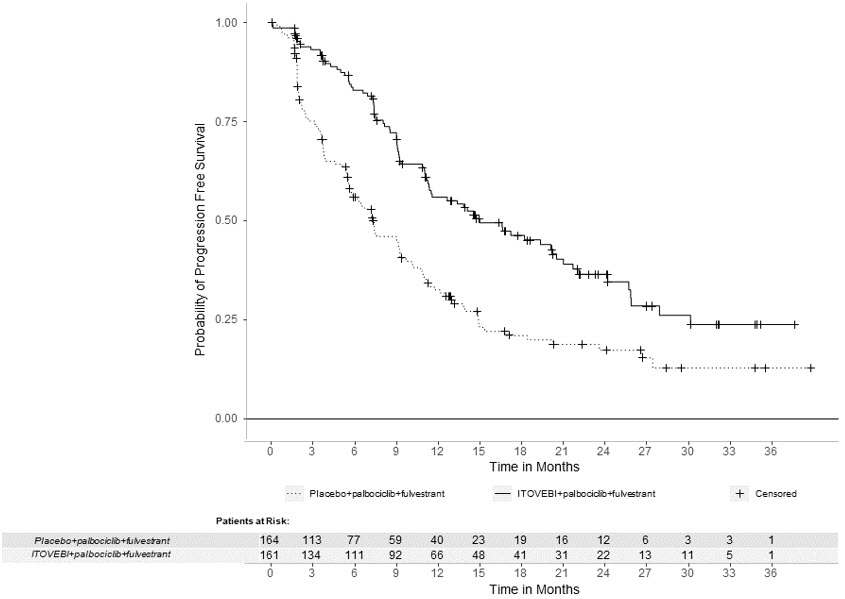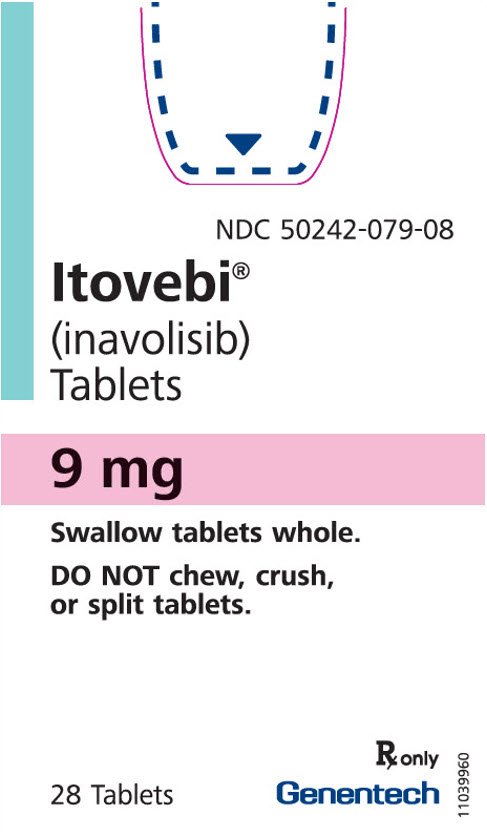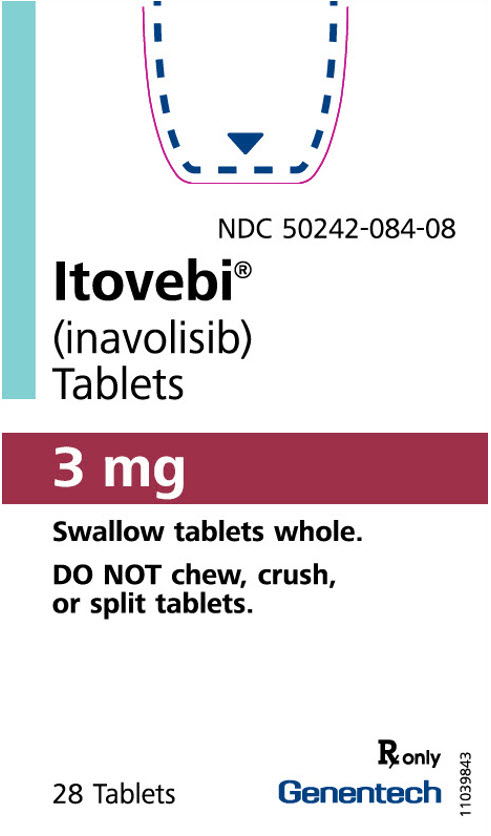 DRUG LABEL: Itovebi
NDC: 50242-079 | Form: TABLET, FILM COATED
Manufacturer: Genentech, Inc.
Category: prescription | Type: HUMAN PRESCRIPTION DRUG LABEL
Date: 20260120

ACTIVE INGREDIENTS: INAVOLISIB 9 mg/1 1
INACTIVE INGREDIENTS: MICROCRYSTALLINE CELLULOSE; LACTOSE MONOHYDRATE; SODIUM STARCH GLYCOLATE TYPE A; MAGNESIUM STEARATE; POLYVINYL ALCOHOL, UNSPECIFIED; POLYETHYLENE GLYCOL, UNSPECIFIED; FERRIC OXIDE YELLOW; TALC; FERRIC OXIDE RED; TITANIUM DIOXIDE

HIGHLIGHTS OF PRESCRIBING INFORMATION

These highlights do not include all the information needed to use ITOVEBI safely and effectively. See full prescribing information for ITOVEBI.
ITOVEBI® (inavolisib) tablets, for oral use
Initial U.S. Approval: 2024

RECENT MAJOR CHANGES

Warnings and Precautions, Hyperglycemia (5.1) | 09/2025

1 INDICATIONS AND USAGE

ITOVEBI is a kinase inhibitor indicated in combination with palbociclib and fulvestrant for the treatment of adults with endocrine-resistant, PIK3CA-mutated, hormone receptor (HR)-positive, human epidermal growth factor receptor 2 (HER2)-negative, locally advanced or metastatic breast cancer, as detected by an FDA-approved test, following recurrence on or after completing adjuvant endocrine therapy. (1, 14.1)

2 DOSAGE AND ADMINISTRATION

- Select patients for the treatment of HR-positive, HER2-negative, locally advanced or metastatic breast cancer with ITOVEBI based on the presence of one or more PIK3CA mutations in plasma specimen. (2.1)
- Recommended dosage: 9 mg orally once daily with or without food. (2.3)
- See Full Prescribing Information for dosage modifications of ITOVEBI due to adverse reactions. (2.4)
- Reduce the starting dose in patients with moderate renal impairment. (2.5)

3 DOSAGE FORMS AND STRENGTHS

Tablets: 3 mg and 9 mg (3)

4 CONTRAINDICATIONS

None. (4)

5 WARNINGS AND PRECAUTIONS

- Hyperglycemia: ITOVEBI can cause severe or fatal hyperglycemia including ketoacidosis. Before initiating treatment with ITOVEBI, test fasting plasma glucose (FPG), HbA1c, and optimize blood glucose. Initiate or optimize anti-hyperglycemic medications as clinically indicated. Interrupt, reduce dose, or discontinue ITOVEBI if severe hyperglycemia occurs. (2.4, 5.1)
- Stomatitis: ITOVEBI can cause severe stomatitis. Consider treating with a corticosteroid-containing mouthwash if stomatitis occurs. Monitor patients for signs and symptoms of stomatitis. Withhold, reduce dose, or permanently discontinue ITOVEBI based on severity. (2.4, 5.2)
- Diarrhea: ITOVEBI can cause diarrhea, which may be severe, and result in dehydration and acute kidney injury. Advise patients to start anti-diarrheal treatment, increase oral fluids, and notify their healthcare provider if severe diarrhea occurs. Interrupt, reduce dose, or discontinue ITOVEBI if severe diarrhea occurs. (2.4, 5.3)
- Embryo-Fetal Toxicity: ITOVEBI can cause fetal harm. Advise patients of potential risk to a fetus and to use effective non-hormonal contraception. (5.4, 8.1, 8.3)
  Refer to the Full Prescribing Information of palbociclib and fulvestrant for pregnancy and contraception information.

6 ADVERSE REACTIONS

The most common (≥ 20%) adverse reactions, including laboratory abnormalities, were decreased neutrophils, decreased hemoglobin, increased fasting glucose, decreased platelets, decreased lymphocytes, stomatitis, diarrhea, decreased calcium, fatigue, decreased potassium, increased creatinine, increased ALT, nausea, decreased sodium, decreased magnesium, rash, decreased appetite, COVID-19 infection, and headache. (6.1)

To report SUSPECTED ADVERSE REACTIONS, contact Genentech at 1-888-835-2555 or FDA at 1-800-FDA-1088 or www.fda.gov/medwatch.

8 USE IN SPECIFIC POPULATIONS

Lactation: Advise not to breastfeed. (8.2)

FULL PRESCRIBING INFORMATION

1 INDICATIONS AND USAGE

ITOVEBI, in combination with palbociclib and fulvestrant, is indicated for the treatment of adults with endocrine-resistant, PIK3CA-mutated, hormone receptor (HR)-positive, human epidermal growth factor receptor 2 (HER2)-negative, locally advanced or metastatic breast cancer, as detected by an FDA-approved test, following recurrence on or after completing adjuvant endocrine therapy [see Clinical Studies (14.1)].

2 DOSAGE AND ADMINISTRATION

2.1 Patient Selection

Select patients for the treatment of HR-positive, HER2-negative, locally advanced or metastatic breast cancer with ITOVEBI based on the presence of one or more PIK3CA mutations in plasma specimens [see Clinical Studies (14.1)].

Information on FDA-approved tests for the detection of PIK3CA mutations in breast cancer is available at: http://www.fda.gov/companiondiagnostics.

2.2 Recommended Evaluation Before Initiating ITOVEBI

Evaluate fasting plasma glucose (FPG)/blood glucose (FBG) and hemoglobin A1C (HbA1C) and optimize blood glucose prior to starting ITOVEBI and at regular intervals during treatment [see Warnings and Precautions (5.1)].

2.3 Recommended Dosage

The recommended dosage of ITOVEBI is 9 mg taken orally once daily, with or without food, until disease progression or unacceptable toxicity.

Advise patients to take ITOVEBI at approximately the same time each day.

Swallow ITOVEBI tablet(s) whole. Do not chew, crush, or split prior to swallowing.

If a patient misses a dose, instruct the patient to take the missed dose as soon as possible within 9 hours. After more than 9 hours, instruct the patient to skip the dose and take the next dose at the scheduled time.

If a patient vomits a dose, instruct patients not to take an additional dose on that day and resume the usual dosing schedule the next day.

Administer ITOVEBI in combination with palbociclib and fulvestrant. The recommended dosage of palbociclib is 125 mg taken orally once daily for 21 consecutive days followed by 7 days off treatment to comprise a cycle of 28 days. Refer to the Full Prescribing Information for palbociclib and fulvestrant for dosing information.

For premenopausal and perimenopausal women, administer a luteinizing hormone-releasing hormone (LHRH) agonist in accordance with local clinical practice.

For men, consider administering an LHRH agonist in accordance with local clinical practice.

2.4 Dosage Modifications for Adverse Reactions

The recommended dose reduction levels of ITOVEBI for adverse reactions are listed in Table 1. Permanently discontinue ITOVEBI if patients are unable to tolerate the second dose reduction.

Table 1: Dose Reduction for Adverse Reactions
Dose Level | Dose and Schedule
Recommended starting dose | 9 mg daily
First dose reduction | 6 mg daily
Second dose reduction | 3 mg daily

The recommended dosage modifications of ITOVEBI for adverse reactions are summarized in Table 2.

Table 2: Recommended Dosage Modifications for Adverse Reactions
Adverse Reaction | Severity | Dosage Modification
Hyperglycemia [Before initiating treatment with ITOVEBI, test FPG or FBG, and HbA1C levels, and optimize plasma/blood glucose levels in all patients. After initiating treatment with ITOVEBI, monitor FPG or FBG levels based on the recommended schedule, and as clinically indicated [see Warnings and Precautions (5.1)].] [see Warnings and Precautions (5.1)] | Fasting glucose levels (FPG or FBG) > ULN to 160 mg/dL (> ULN – 8.9 mmol/L) | - No adjustment of ITOVEBI required. - Consider dietary modifications and ensure adequate hydration. - Initiate or intensify oral anti-hyperglycemic medications for patients with risk factors for hyperglycemia.
Hyperglycemia [Before initiating treatment with ITOVEBI, test FPG or FBG, and HbA1C levels, and optimize plasma/blood glucose levels in all patients. After initiating treatment with ITOVEBI, monitor FPG or FBG levels based on the recommended schedule, and as clinically indicated [see Warnings and Precautions (5.1)].] [see Warnings and Precautions (5.1)] | Fasting glucose levels > 160 to 250 mg/dL (> 8.9 – 13.9 mmol/L) | - Withhold ITOVEBI until FPG or FBG ≤ 160 mg/dL (≤ 8.9 mmol/L). - Initiate or intensify anti-hyperglycemic medications. - Resume ITOVEBI at the same dose level. - If FPG or FBG persists > 200 – 250 mg/dL (> 11.1 – 13.9 mmol/L) for 7 days under appropriate anti-hyperglycemic treatment, consider consultation with a healthcare professional experienced in the treatment of hyperglycemia.
Hyperglycemia [Before initiating treatment with ITOVEBI, test FPG or FBG, and HbA1C levels, and optimize plasma/blood glucose levels in all patients. After initiating treatment with ITOVEBI, monitor FPG or FBG levels based on the recommended schedule, and as clinically indicated [see Warnings and Precautions (5.1)].] [see Warnings and Precautions (5.1)] | Fasting glucose levels > 250 to 500 mg/dL (> 13.9 – 27.8 mmol/L) | - Withhold ITOVEBI. - Initiate or intensify anti-hyperglycemic medications. - Administer appropriate hydration if required. - If FPG or FBG decreases to ≤ 160 mg/dL (≤ 8.9 mmol/L) within 7 days, resume ITOVEBI at the same dose level. - If FPG or FBG decreases to ≤ 160 mg/dL (≤ 8.9 mmol/L) in ≥ 8 days, resume ITOVEBI at one lower dose level. - If FPG or FBG > 250 to 500 mg/dL (> 13.9 – 27.8 mmol/L) recurs within 30 days, withhold ITOVEBI until FPG or FBG decreases to ≤ 160 mg/dL (≤ 8.9 mmol/L). Resume ITOVEBI at one lower dose level.
Hyperglycemia [Before initiating treatment with ITOVEBI, test FPG or FBG, and HbA1C levels, and optimize plasma/blood glucose levels in all patients. After initiating treatment with ITOVEBI, monitor FPG or FBG levels based on the recommended schedule, and as clinically indicated [see Warnings and Precautions (5.1)].] [see Warnings and Precautions (5.1)] | Fasting glucose levels > 500 mg/dL (> 27.8 mmol/L) | - Withhold ITOVEBI. - Initiate or intensify anti-hyperglycemic medications. - Assess for volume depletion and ketosis and administer appropriate hydration. - If FPG or FBG decreases to ≤ 160 mg/dL (≤ 8.9 mmol/L), resume ITOVEBI at one lower dose level. - If FPG or FBG > 500 mg/dL (> 27.8 mmol/L) recurs within 30 days, permanently discontinue ITOVEBI.
Stomatitis [see Warnings and Precautions (5.2)] | Grade 1 [Based on CTCAE version 5.0.] | - No adjustment of ITOVEBI required. - Initiate or intensify appropriate medical therapy (e.g., corticosteroid-containing mouthwash) as clinically indicated.
Stomatitis [see Warnings and Precautions (5.2)] | Grade 2 | - Withhold ITOVEBI until recovery to Grade ≤ 1. - Initiate or intensify appropriate medical therapy. Resume ITOVEBI at the same dose level. - For recurrent Grade 2 stomatitis, withhold ITOVEBI until recovery to Grade ≤ 1, then resume ITOVEBI at one lower dose level.
Stomatitis [see Warnings and Precautions (5.2)] | Grade 3 | - Withhold ITOVEBI until recovery to Grade ≤ 1. - Initiate or intensify appropriate medical therapy. Resume ITOVEBI at one lower dose level.
Stomatitis [see Warnings and Precautions (5.2)] | Grade 4 | - Permanently discontinue ITOVEBI.
Diarrhea [see Warnings and Precautions (5.3)] | Grade 1 | - No adjustment of ITOVEBI required. - Initiate appropriate medical therapy and monitor as clinically indicated.
Diarrhea [see Warnings and Precautions (5.3)] | Grade 2 | - Withhold ITOVEBI until recovery to Grade ≤ 1, then resume ITOVEBI at the same dose level. - Initiate or intensify appropriate medical therapy and monitor as clinically indicated. - For recurrent Grade 2 diarrhea, withhold ITOVEBI until recovery to Grade ≤ 1, then resume ITOVEBI at one lower dose level.
Diarrhea [see Warnings and Precautions (5.3)] | Grade 3 | - Withhold ITOVEBI until recovery to Grade ≤ 1, then resume ITOVEBI at one lower dose level. - Initiate or intensify appropriate medical therapy and monitor as clinically indicated.
Diarrhea [see Warnings and Precautions (5.3)] | Grade 4 | - Permanently discontinue ITOVEBI.
Hematologic Toxicities [see Adverse Reactions (6.1)] | Grade 1, 2, or 3 | - No adjustment of ITOVEBI required. - Monitor complete blood count and for signs or symptoms of hematologic toxicities as clinically indicated.
Hematologic Toxicities [see Adverse Reactions (6.1)] | Grade 4 | - Withhold ITOVEBI until recovery to Grade ≤ 2. - Resume ITOVEBI at the same dose level or reduce to one lower dose level as clinically indicated.
Other Adverse Reactions [see Adverse Reactions (6.1)] | Grade 1 | - No adjustment of ITOVEBI required.
Other Adverse Reactions [see Adverse Reactions (6.1)] | Grade 2 | - Consider withholding ITOVEBI, if clinically indicated, until recovery to Grade ≤ 1. - Resume ITOVEBI at the same dose level.
Other Adverse Reactions [see Adverse Reactions (6.1)] | Grade 3 (first event) | - Withhold ITOVEBI until recovery to Grade ≤ 1. - Resume ITOVEBI at the same dose level or one lower dose level based on clinical evaluation.
Other Adverse Reactions [see Adverse Reactions (6.1)] | Grade 3 (recurrent) | - Withhold ITOVEBI until recovery to Grade ≤ 1. - Resume ITOVEBI at one lower dose level.
Other Adverse Reactions [see Adverse Reactions (6.1)] | Grade 4 | - Permanently discontinue ITOVEBI.

2.5 Dosage Modification for Moderate Renal Impairment

The recommended starting dosage of ITOVEBI for patients with moderate renal impairment (eGFR 30 to < 60 mL/min based on CKD-EPI) is 6 mg orally once daily [see Use in Specific Populations (8.6) and Clinical Pharmacology (12.3)].

3 DOSAGE FORMS AND STRENGTHS

Tablets:

- 3 mg: red and round convex-shaped with an "INA 3" debossing on one side.
- 9 mg: pink and oval-shaped with an "INA 9" debossing on one side.

4 CONTRAINDICATIONS

None.

5 WARNINGS AND PRECAUTIONS

5.1 Hyperglycemia

Severe or fatal hyperglycemia, including ketoacidosis, can occur in patients treated with ITOVEBI. Ketoacidosis with a fatal outcome has occurred in the postmarketing setting.

Increased fasting glucose occurred in 85% of patients treated with ITOVEBI, including 22% of patients with Grade 2 (FPG > 160 to 250 mg/dL), 12% with Grade 3 (FPG > 250 to 500 mg/dL), and 0.6% with Grade 4 (FPG > 500 mg/dL) events.

In INAVO120, 46% (74/162) of patients who received ITOVEBI were treated with oral anti-hyperglycemic medications and 7% (11/162) were treated with insulin to manage increased fasting glucose. In patients who experienced increased fasting glucose of > 160 mg/dL, 96% (52/54) had an improvement in fasting glucose of at least one grade level with a median time to improvement of 8 days (range: 2 to 43 days).

Among patients with hyperglycemia, the median time to first onset was 7 days (range: 2 to 955 days). Hyperglycemia led to dose interruption in 28%, to dose reduction in 2.5%, and to discontinuation of ITOVEBI in 1.2% of patients.

The safety of ITOVEBI in patients with Type 1 diabetes mellitus, or Type 2 diabetes mellitus requiring ongoing anti-hyperglycemic treatment have not been studied.

Before initiating treatment with ITOVEBI, test fasting glucose levels (FPG or FBG), HbA1C levels, and optimize fasting glucose.

After initiating treatment with ITOVEBI, or in patients who experience hyperglycemia after initiating treatment with ITOVEBI, monitor or self-monitor fasting glucose levels once every 3 days for the first week (Day 1 to 7), then once every week for the next 3 weeks (Day 8 to 28), then once every 2 weeks for the next 8 weeks, then once every 4 weeks thereafter, and as clinically indicated. Monitor HbA1C every 3 months and as clinically indicated.

Manage hyperglycemia with anti-hyperglycemic medications as clinically indicated. During treatment with anti-hyperglycemic medication, continue monitoring fasting glucose levels. Patients with a history of well-controlled Type 2 diabetes mellitus may require intensified anti-hyperglycemic treatment and close monitoring of fasting glucose levels.

Consider consultation with a healthcare professional experienced in the treatment of hyperglycemia, and initiation of fasting glucose monitoring at home for patients who have risk factors for hyperglycemia or who experience hyperglycemia. Advise patients of the signs and symptoms of hyperglycemia and counsel patients on lifestyle changes.

Based on the severity of the hyperglycemia, ITOVEBI may require dose interruption, reduction, or discontinuation [see Dosage and Administration (2.4)].

5.2 Stomatitis

Severe stomatitis can occur in patients treated with ITOVEBI.

Stomatitis occurred in 51% of patients treated with ITOVEBI in combination with palbociclib and fulvestrant, including Grade 3 events in 6% of patients. The median time to first onset was 13 days (range: 1 to 610 days).

Stomatitis led to dose interruption in 10%, to dose reduction in 3.7%, and to discontinuation of ITOVEBI in 0.6% of patients.

In patients who received ITOVEBI in combination with palbociclib and fulvestrant, 38% used a mouthwash containing corticosteroid for management or prophylaxis of stomatitis.

Monitor patients for signs and symptoms of stomatitis. Withhold, reduce dose, or permanently discontinue ITOVEBI based on severity [see Dosage and Administration (2.4)].

5.3 Diarrhea

Severe diarrhea, including dehydration and acute kidney injury, can occur in patients treated with ITOVEBI.

Diarrhea occurred in 48% of patients treated with ITOVEBI in combination with palbociclib and fulvestrant, including Grade 3 events in 3.7% of patients. The median time to first onset was 15 days (range: 2 to 602 days).

Diarrhea led to dose interruptions in 7% of patients, and dose reductions in 1.2% of patients. Anti-diarrheal medicines were used in 28% (46/162) of patients who received ITOVEBI in combination with palbociclib and fulvestrant to manage symptoms.

Monitor patients for signs and symptoms of diarrhea. Advise patients to increase oral fluids and start anti-diarrheal treatment at the first sign of diarrhea while taking ITOVEBI. Withhold, reduce dose, or permanently discontinue ITOVEBI based on severity [see Dosage and Administration (2.4)].

5.4 Embryo-Fetal Toxicity

Based on findings in animals and its mechanism of action, ITOVEBI can cause fetal harm when administered to a pregnant woman [see Clinical Pharmacology (12.1)]. In an animal reproduction study, oral administration of inavolisib to pregnant rats during the period of organogenesis caused adverse developmental outcomes, including embryo-fetal mortality, structural abnormalities, and alterations to growth at maternal exposures approximately equivalent to the human exposure at the recommended dose of 9 mg/day based on area under the curve (AUC).

Advise pregnant women and females of reproductive potential of the potential risk to a fetus. Advise females of reproductive potential to use effective non-hormonal contraception during treatment with ITOVEBI and for 1 week after the last dose. Advise male patients with female partners of reproductive potential to use effective contraception during treatment with ITOVEBI and for 1 week after the last dose [see Use in Specific Populations (8.1 and 8.3)].

ITOVEBI is used in combination with palbociclib and fulvestrant. Refer to the Full Prescribing Information of palbociclib and fulvestrant for pregnancy and contraception information.

6 ADVERSE REACTIONS

The following adverse reactions are discussed in greater detail in other sections of the label:

- Hyperglycemia [see Warnings and Precautions (5.1)]
- Stomatitis [see Warnings and Precautions (5.2)]
- Diarrhea [see Warnings and Precautions (5.3)]

6.1 Clinical Trial Experience

Because clinical trials are conducted under widely varying conditions, adverse reaction rates observed in the clinical trials of a drug cannot be directly compared to rates in the clinical trials of another drug and may not reflect the rates observed in practice.

Locally Advanced or Metastatic Breast Cancer

INAVO120

The safety of ITOVEBI was evaluated in a randomized, double-blind, placebo-controlled study (INAVO120) in 324 patients with PIK3CA-mutated, HR-positive, HER2-negative, locally advanced or metastatic breast cancer [see Clinical Studies (14.1)].

Patients received either ITOVEBI 9 mg (n=162) or placebo (n=162) with palbociclib and fulvestrant. The median duration of treatment with ITOVEBI was 9 months (range: 0 to 39 months) in the ITOVEBI with palbociclib and fulvestrant arm.

Serious adverse reactions occurred in 24% of patients who received ITOVEBI with palbociclib and fulvestrant. Serious adverse reactions in ≥ 1% of patients included anemia (1.9%), diarrhea (1.2%), and urinary tract infection (1.2%).

Fatal adverse reactions occurred in 3.7% of patients who received ITOVEBI with palbociclib and fulvestrant, including (0.6% each) acute coronary syndrome, cerebral hemorrhage, cerebrovascular accident, COVID-19 infection, and gastrointestinal hemorrhage.

Permanent discontinuation of ITOVEBI due to an adverse reaction occurred in 6% of patients. Adverse reactions which resulted in permanent discontinuation of ITOVEBI included hyperglycemia (1.2%), and (0.6% each) stomatitis, gastric ulcer, intestinal perforation, anal abscess, increased ALT, decreased weight, bone pain, musculoskeletal pain, transitional cell carcinoma, and acute kidney injury.

Dosage interruptions of ITOVEBI due to an adverse reaction occurred in 69% of patients. Adverse reactions which required dosage interruption in ≥ 2% of patients included hyperglycemia (28%), neutropenia (23%), COVID-19 infection (16%), stomatitis (10%), diarrhea (7%), thrombocytopenia (4.9%), anemia (4.3%), upper respiratory tract infection (4.3%), decreased white blood cell count (3.7%), pyrexia (3.1%), nausea (2.5%), and fatigue (2.5%).

Dose reductions of ITOVEBI due to adverse reactions occurred in 14% of patients. Adverse reactions which required dose reduction of ITOVEBI in ≥ 2% of patients were stomatitis (3.7%) and hyperglycemia (2.5%).

The most common (≥ 20%) adverse reactions, including laboratory abnormalities, were decreased neutrophils, decreased hemoglobin, increased fasting glucose, decreased platelets, decreased lymphocytes, stomatitis, diarrhea, decreased calcium, fatigue, decreased potassium, increased creatinine, increased ALT, nausea, decreased sodium, decreased magnesium, rash, decreased appetite, COVID-19 infection, and headache.

Adverse reactions and laboratory abnormalities in INAVO120 are summarized in Table 3 and Table 4, respectively. Patient-reported symptoms are summarized in Table 5.

Table 3: Adverse Reactions (≥ 10% with ≥ 5% [All Grades] or ≥ 2% [Grade 3-4] Higher Incidence in the ITOVEBI Arm) in INAVO120
Adverse Reaction | ITOVEBI + Palbociclib + Fulvestrant N=162 |  | Placebo + Palbociclib + Fulvestrant N=162
Adverse Reaction | All Grades (%) | Grade 3-4 (%) | All Grades (%) | Grade 3-4 (%)
Gastrointestinal Disorders
Stomatitis [Includes aphthous ulcer, glossitis, glossodynia, lip ulceration, mouth ulceration, mucosal inflammation, and stomatitis.] | 51 | 6 [No Grade 4 adverse reactions were observed.] | 27 | 0
Diarrhea | 48 | 3.7 | 16 | 0
Nausea | 28 | 0.6 | 17 | 0
Vomiting | 15 | 0.6 | 5 | 1.2
General Disorders and Administration Site Conditions
Fatigue | 38 | 1.9 | 25 | 1.2
Skin and Subcutaneous Tissue Disorders
Rash [Includes other related terms.] | 26 | 0 | 19 | 0
Alopecia | 19 | 0 | 6 | 0
Dry skin [Includes dry skin, skin fissures, xerosis, and xeroderma.] | 13 | 0 | 4.3 | 0
Metabolism and Nutrition Disorders
Decreased appetite | 24 | 0 | 9 | 0
Infections and Infestations
COVID-19 infection | 23 | 1.9 | 11 | 0.6
Urinary tract infection | 15 | 1.2 | 9 | 0
Nervous System Disorders
Headache | 22 | 0 | 14 | 0
Investigations
Decreased weight | 17 | 3.7 | 0.6 | 0

Clinically relevant adverse reactions occurring in < 10% of patients who received ITOVEBI in combination with palbociclib and fulvestrant included abdominal pain, dry eye, dysgeusia, and dyspepsia.

Table 4: Select Laboratory Abnormalities (≥ 10% with a ≥ 2% [All Grades or Grade 3-4] Higher Incidence in the ITOVEBI Arm) in INAVO120
Laboratory Abnormality | ITOVEBI + Palbociclib + Fulvestrant [The denominator used to calculate the rate varied from 122 to 160 based on the number of patients with a baseline value and at least one post-treatment value.] |  | Placebo + Palbociclib + Fulvestrant [The denominator used to calculate the rate varied from 131 to 161 based on the number of patients with a baseline value and at least one post-treatment value.]
Laboratory Abnormality | All Grades (%) | Grade 3-4 (%) | All Grades (%) | Grade 3-4 (%)
Hematology
Neutrophils (total, absolute) decreased | 95 | 82 | 97 | 79
Hemoglobin decreased | 88 | 8 [No Grade 4 laboratory abnormalities were observed.] | 85 | 2.5
Platelets decreased | 84 | 16 | 71 | 3.7
Lymphocytes (absolute) decreased | 72 | 9 | 68 | 14
Chemistry
Glucose (fasting) increased [Grading according to CTCAE version 4.03.] | 85 | 12 | 43 | 0
Calcium decreased | 42 | 3.1 | 32 | 3.7
Potassium decreased | 38 | 6 | 21 | 0.6
Creatinine increased | 38 | 1.9 | 30 | 1.2
ALT increased | 34 | 3.1 | 29 | 1.2
Sodium decreased | 28 | 2.5 | 19 | 2.5
Magnesium decreased | 27 | 0.6 | 21 | 0
Lipase (fasting) increased | 16 | 1.4 | 7 | 0
ALT = alanine aminotransferase

In INAVO120, patient-reported symptomatic toxicities (i.e., diarrhea, nausea, vomiting, fatigue, mouth sores, decreased appetite, and rash) were assessed via the Patient-Reported Outcomes – Common Terminology Criteria for Adverse Events (PRO-CTCAE) at baseline, every two weeks through Cycle 3 Day 15, and then Day 1 of every other 28-day cycle until treatment discontinuation.

Completion rates in both arms were > 90% at baseline and > 80% at subsequent time points where > 50% of randomized patients were on treatment.

Table 5: Patient-Reported Symptoms Assessed by PRO-CTCAE in INAVO120
Symptom (Attribute) [The symptom attribute scoring is defined by amount/frequency/severity with a score of 0 = 'not at all'/'never'/'none'; 1 = 'a little bit'/'rarely'/'mild'; 2 = 'somewhat'/'occasionally'/'moderate'; 3 = 'quite a bit'/'frequently'/'severe'; 4 = 'very much'/'almost constantly'/'very severe'.] | Any Symptom Before Treatment (%) [The percentage of patients whose symptom score before treatment was 1-4.] |  |  | Any Worsening on Treatment (%) [The percentage of patients whose symptom score increased during treatment, with respect to their score before treatment.] |  | Worsening to Score 3 or 4 (%) [The percentage of patients whose symptom score increased to 3 or 4 during treatment, with respect to their score before treatment.]
Symptom (Attribute) [The symptom attribute scoring is defined by amount/frequency/severity with a score of 0 = 'not at all'/'never'/'none'; 1 = 'a little bit'/'rarely'/'mild'; 2 = 'somewhat'/'occasionally'/'moderate'; 3 = 'quite a bit'/'frequently'/'severe'; 4 = 'very much'/'almost constantly'/'very severe'.] | ITOVEBI + P + F (N=148) [The number of patients who provided a score before treatment and at least one on-treatment score.] | Placebo + P + F (N=152) |  | ITOVEBI + P + F (N=148) | Placebo + P + F (N=152) | ITOVEBI + P + F (N=148) |  | Placebo + P + F (N=152)
Diarrhea (frequency), % | 23 | 15 |  | 78 | 49 | 32 |  | 8
Nausea (frequency), % | 21 | 21 |  | 59 | 50 | 20 |  | 11
Vomiting (frequency), % | 9 | 6 |  | 35 | 26 | 6 |  | 3.3
Fatigue (severity), % | 72 | 69 |  | 72 | 58 | 32 |  | 22
Mouth sores (severity), % | 11 | 14 |  | 74 | 52 | 30 |  | 9
Decreased appetite (severity), % | 38 | 28 |  | 78 | 55 | 26 |  | 12
Symptom (Attribute) | Baseline Presence |  |  |  | Post-baseline Presence
Symptom (Attribute) | ITOVEBI + P + F (N=148) |  | Placebo + P + F (N=152) |  | ITOVEBI + P + F (N=148) |  | Placebo + P + F (N=152)
Rash (yes), % | 5 |  | 5 |  | 50 |  | 38
ITOVEBI+P+F = ITOVEBI with palbociclib and fulvestrant arm; Placebo+P+F = placebo with palbociclib and fulvestrant arm.

Patient-reported overall side-effect impact was assessed using the Modified Bother Item (MBI). Patients provided a response to "I am bothered by side effects of treatment," and at baseline the proportion of patients with MBI responses of "not at all" were 70% in the ITOVEBI with palbociclib and fulvestrant arm and 76% in the placebo with palbociclib and fulvestrant arm. At Cycle 2 Day 15, the proportion of patients with MBI responses of "not at all" were 25% in the ITOVEBI with palbociclib and fulvestrant arm and 53% in the placebo with palbociclib and fulvestrant arm. Through 31 cycles of treatment, patients in the ITOVEBI with palbociclib and fulvestrant arm reported more side effect bother compared to the placebo with palbociclib and fulvestrant arm.

6.2 Postmarketing Experience

The following adverse reactions have been identified during post-approval use of ITOVEBI. Because these reactions are reported voluntarily from a population of uncertain size, it is not always possible to reliably estimate their frequency or establish a causal relationship to drug exposure.

Metabolism and Nutrition Disorders: Ketoacidosis

8 USE IN SPECIFIC POPULATIONS

8.1 Pregnancy

Risk Summary

ITOVEBI is used in combination with palbociclib and fulvestrant. Refer to the Full Prescribing Information of palbociclib and fulvestrant for pregnancy information.

Based on animal data and its mechanism of action, ITOVEBI can cause fetal harm when administered to a pregnant woman [see Clinical Pharmacology (12.1)]. There are no available data on the use of ITOVEBI in pregnant women to inform a drug-associated risk. In an animal reproduction study, oral administration of inavolisib to pregnant rats during the period of organogenesis caused adverse developmental outcomes, including embryo-fetal mortality, structural abnormalities, and alterations to growth at maternal exposures approximately equivalent to the human exposure at the recommended dose of 9 mg/day based on AUC (see Data). Advise pregnant women and females of reproductive potential of the potential risk to a fetus.

The background risk of major birth defects and miscarriage for the indicated population is unknown. In the U.S. general population, the estimated background risk of major birth defects is 2% to 4% and of miscarriage is 15% to 20% of clinically recognized pregnancies in the U.S. general population.

Data

Animal Data

In an embryo-fetal development study, pregnant rats received oral doses of inavolisib up to 6 mg/kg/day during the period of organogenesis. Administration of doses ≥ 2 mg/kg/day resulted in decreases in fetal body weight and placental weight, post-implantation loss, lower fetal viability, fetal malformations (including kyphosis of vertebral column, fused thoracic arch, microphthalmia) and variations (including dilated renal pelvis, short supernumerary rib, wavy rib). At a dose of 2 mg/kg/day, maternal exposures were 0.9 times the human exposure at the recommended dose of 9 mg/day based on AUC.

8.2 Lactation

Risk Summary

ITOVEBI is used in combination with palbociclib and fulvestrant. Refer to the Full Prescribing Information of palbociclib and fulvestrant for lactation information.

There are no data on the presence of inavolisib or its metabolites in human milk, its effects on milk production or a breastfed child. Because of the potential for serious adverse reactions in a breastfed child, advise lactating women to not breastfeed during treatment with ITOVEBI and for 1 week after the last dose.

8.3 Females and Males of Reproductive Potential

ITOVEBI is used in combination with palbociclib and fulvestrant. Refer to the Full Prescribing Information of palbociclib and fulvestrant for contraception and infertility information.

ITOVEBI can cause fetal harm when administered to a pregnant woman [see Use in Specific Populations (8.1)].

Pregnancy Testing

Verify pregnancy status in females of reproductive potential prior to initiating treatment with ITOVEBI.

Contraception

Females

Advise females of reproductive potential to use effective non-hormonal contraception during treatment with ITOVEBI and for 1 week after the last dose.

Males

Advise male patients with female partners of reproductive potential to use effective contraception during treatment with ITOVEBI and for 1 week after the last dose.

Infertility

Based on animal studies, ITOVEBI may impair fertility in females and males of reproductive potential [see Nonclinical Toxicology (13.1)].

8.4 Pediatric Use

The safety and efficacy of ITOVEBI in pediatric patients have not been established.

8.5 Geriatric Use

Of the 162 patients who received ITOVEBI in INAVO120, 15% were ≥ 65 years of age, and 3% were ≥ 75 years of age.

Dosage modifications or interruptions of ITOVEBI due to adverse reactions occurred at a higher incidence for patients ≥ 65 years of age compared to younger patients (79% versus 68%, respectively).

Clinical studies of ITOVEBI did not include sufficient numbers of patients ≥ 65 years of age to determine whether they respond differently from younger patients.

8.6 Renal Impairment

Reduce the dosage in patients with moderate renal impairment (eGFR 30 to < 60 mL/min based on CKD-EPI) [see Dosage and Administration (2.5)]. No dosage modification is recommended in patients with mild renal impairment (eGFR 60 to < 90 mL/min). ITOVEBI has not been evaluated in patients with severe renal impairment (eGFR < 30 mL/min).

11 DESCRIPTION

ITOVEBI contains inavolisib, a kinase inhibitor. The chemical name of inavolisib is (2S)-2-[[2-[(4S)-4-(difluoromethyl)-2-oxo-oxazolidin-3-yl]-5,6-dihydroimidazo[1,2-d][1,4]benzoxazepin-9-yl]amino]propanamide. Inavolisib is a white to off-white, greyish pink, greyish orange, or greyish yellow powder or powder with lumps. Inavolisib demonstrates pH-dependent aqueous solubility; the greatest solubility is at low pH, and solubility decreases with increasing pH. The molecular formula for inavolisib is C18H19F2N5O4 and the molecular weight is 407.37 g/mol. The chemical structure of inavolisib is shown below:

ITOVEBI film-coated tablets are supplied for oral administration with two strengths that contain 3 mg and 9 mg of inavolisib. The tablets also contain lactose, magnesium stearate, microcrystalline cellulose, and sodium starch glycolate. The film-coating contains the following inactive ingredients: polyvinyl alcohol (partially hydrolyzed), titanium dioxide, macrogol/polyethylene glycol, talc, iron oxide red, and iron oxide yellow (in the 9 mg tablet only).

12 CLINICAL PHARMACOLOGY

12.1 Mechanism of Action

Inavolisib is an inhibitor of phosphatidylinositol 3-kinase (PI3K) with inhibitory activity predominantly against PI3Kα. In vitro, inavolisib induced the degradation of mutated PI3K catalytic alpha subunit p110α (encoded by the PIK3CA gene), inhibited phosphorylation of the downstream target AKT, reduced cellular proliferation, and induced apoptosis in PIK3CA-mutated breast cancer cell lines. In vivo, inavolisib reduced tumor growth in PIK3CA-mutated, estrogen receptor-positive, breast cancer xenograft models. The combination of inavolisib with palbociclib and fulvestrant increased tumor growth inhibition compared to each treatment alone or the doublet combinations.

12.2 Pharmacodynamics

Exposure-Response Relationships

The exposure-response relationship for the efficacy of inavolisib has not been fully characterized. Inavolisib time course of pharmacodynamic response is unknown. Higher systemic exposure of inavolisib was associated with higher incidence of Grade ≥ 2 anemia, Grade ≥ 2 hyperglycemia, and inavolisib dosage modifications due to adverse reactions.

Cardiac Electrophysiology

At the recommended approved dosage, a mean increase in the QTc interval of > 20 ms is unlikely.

12.3 Pharmacokinetics

Inavolisib pharmacokinetics are presented as geometric mean (geometric coefficient of variation [geo CV]%) following administration of the approved recommended dosage unless otherwise specified. The inavolisib steady-state AUC is 1,010 h*ng/mL (25%) and Cmax is 69 ng/mL (27%). Steady-state concentrations are predicted to be attained by day 5.

Inavolisib accumulation is approximately 2-fold.

Inavolisib steady-state AUC is proportional with dose from 6 to 12 mg (0.7 to 1.3 times the approved recommended dosage).

Absorption

Inavolisib absolute oral bioavailability is 76%. Inavolisib steady-state median (min, max) time to maximum plasma concentration (Tmax) is 3 hours (0.5, 4 hours).

Effect of Food

No clinically significant differences in inavolisib pharmacokinetics were observed following administration of inavolisib with a high-fat meal (approximately 1,000 calories, 50% fat).

Distribution

Inavolisib apparent (oral) volume of distribution is 155 L (26%). Inavolisib plasma protein binding is 37% and is not concentration-dependent in vitro. Inavolisib blood-to-plasma ratio is 0.8.

Elimination

Inavolisib elimination half-life is 15 hours (24%) with a total clearance of 8.8 L/hr (29%).

Metabolism

Inavolisib is primarily metabolized by hydrolysis. In vitro, inavolisib was minimally metabolized by CYP3A.

Excretion

Following oral administration of a single radiolabeled dose, 49% of the administered dose was recovered in urine (40% unchanged) and 48% in feces (11% unchanged).

Specific Populations

No clinically significant differences in the pharmacokinetics of inavolisib were observed based on age (27 to 85 years), sex, race (Asian or White), body weight (39 to 159 kg), or mild hepatic impairment (total bilirubin > ULN to ≤ 1.5 × ULN or AST > ULN and total bilirubin ≤ ULN). The effect of moderate to severe hepatic impairment on inavolisib pharmacokinetics is unknown.

Patients with Renal Impairment

Inavolisib AUC was 73% higher in patients with moderate renal impairment compared to patients with normal renal function (eGFR ≥ 90 mL/min).

No clinically significant differences in the pharmacokinetics of inavolisib were observed in patients with mild renal impairment compared to patients with normal renal function. The effect of severe renal impairment (eGFR < 30 mL/min) on the pharmacokinetics of inavolisib is unknown.

Drug Interaction Studies

Clinical Studies and Model-Informed Approaches

Proton Pump Inhibitors: No clinically significant difference in steady-state inavolisib pharmacokinetics were observed based upon concomitant use of a proton pump inhibitor (lansoprazole, omeprazole, esomeprazole, pantoprazole, or rabeprazole).

In Vitro Studies

CYP450 Enzymes: Inavolisib induces CYP3A and CYP2B6. Inavolisib is a time-dependent inhibitor of CYP3A. Inavolisib does not inhibit CYP1A2, CYP2B6, CYP2C8, CYP2C9, CYP2C19, or CYP2D6.

Transporter Systems: Inavolisib is a substrate of P-glycoprotein (P-gp) and breast cancer resistance protein (BCRP), but is not a substrate of OATP1B1, OATP1B3, OCT1, OCT2, MATE1, MATE2K, OAT1, OAT2. Inavolisib does not inhibit P-gp, BCRP, OATP1B1, OATP1B3, OCT1, OCT2, OAT1, OAT3, MATE1, or MATE2K.

13 NONCLINICAL TOXICOLOGY

13.1 Carcinogenesis, Mutagenesis, Impairment of Fertility

Carcinogenicity studies with inavolisib have not been conducted.

Inavolisib was not mutagenic in the bacterial reverse mutation (Ames) assay. Inavolisib was clastogenic in an in vitro human lymphocyte micronucleus assay. Inavolisib was not genotoxic in an in vivo rat bone marrow micronucleus test and did not induce DNA break in a liver comet assay.

Fertility studies with inavolisib have not been conducted. In repeat-dose toxicity studies, inavolisib was administered orally once daily for up to 3 months duration in rats and dogs.

In male rats, dose-dependent atrophy of the prostate and seminal vesicle and decreased organ weights of the prostate, seminal vesicle, epididymis and testis were observed at doses ≥ 1.5 mg/kg/day (≥ 0.4 times the human exposure at the recommended dose of 9 mg/day based on AUC). In male dogs, focal inspissation of seminiferous tubule contents and multinucleated spermatids in the testis and epithelial degeneration/necrosis in the epididymis were observed following 4 weeks of dosing at ≥ 1.5 mg/kg/day (≥ 2 times the human exposure at the recommended dose of 9 mg/day based on AUC) and decreased sperm count was observed following 3 months of dosing at ≥ 1 mg/kg/day (≥ 1.2 times the human exposure at the recommended dose of 9 mg/day based on AUC). Findings in dogs were not observed following a recovery period.

In female rats, atrophy in the uterus and vagina, decreased ovarian follicles, and findings suggestive of an interruption/alteration of the estrous cycle were observed following up to 3 months of dosing at doses ≥ 3 mg/kg/day (≥ 1.2 times the human exposure at the recommended dose of 9 mg/day based on AUC). Findings in the uterus, vagina, and estrous cycle observed in the 4-week toxicity study were not observed following recovery. Recovery was not assessed in the 3-month study in rats.

13.2 Animal Toxicology and/or Pharmacology

Lens degeneration, characterized by lens fiber swelling, separation of lens fibers, and/or accumulation of subcapsular proteinaceous material, was observed in rats at an oral inavolisib dose of 10 mg/kg/day (6.3 times the human exposure at the recommended dose of 9 mg/day based on AUC). In dogs, lens fiber swelling and lens cortex vacuolation were observed at oral inavolisib doses ≥ 0.3 mg/kg/day (≥ 0.5 times the human exposure at the recommended dose based on AUC) and ≥ 1 mg/kg/day (≥ 1.2 times the human exposure at the recommended dose based on AUC), respectively. Lens degeneration was present in rats following a 4-week recovery period but was not present in dogs following a 12-week recovery period.

14 CLINICAL STUDIES

14.1 Locally Advanced or Metastatic Breast Cancer

INAVO120

INAVO120 (NCT04191499) was a randomized (1:1), double-blind, placebo-controlled trial evaluating the efficacy of ITOVEBI in combination with palbociclib and fulvestrant in adult patients with endocrine-resistant PIK3CA-mutated, HR-positive, HER2-negative (defined as IHC 0 or 1+, or IHC 2+/ISH-), locally advanced or metastatic breast cancer whose disease progressed during or within 12 months of completing adjuvant endocrine therapy and who have not received prior systemic therapy for locally advanced or metastatic disease. Randomization was stratified by presence of visceral disease (yes or no), endocrine resistance (primary or secondary), and geographic region (North America/Western Europe, Asia, other).

Primary endocrine resistance was defined as relapse while on the first 2 years of adjuvant endocrine therapy (ET) and secondary endocrine resistance was defined as relapse while on adjuvant ET after at least 2 years or relapse within 12 months of completing adjuvant ET.

Patients were required to have HbA1C < 6% and fasting blood glucose < 126 mg/dL. The study excluded patients with Type 1 diabetes mellitus or Type 2 diabetes mellitus requiring ongoing anti-hyperglycemic treatment at the start of study treatment.

PIK3CA mutation status was prospectively determined in a central laboratory using the FoundationOne® Liquid CDx assay on plasma-derived circulating tumor DNA (ctDNA) or in local laboratories using various validated polymerase chain reaction (PCR) or next-generation sequencing (NGS) assays on tumor tissue or plasma. All patients were required to provide both a freshly collected pre-treatment blood sample and a tumor tissue sample for central evaluation and determination of PIK3CA mutation(s) status.

Patients received either ITOVEBI 9 mg (n=161) or placebo (n=164) orally once daily, in combination with palbociclib 125 mg orally once daily for 21 consecutive days followed by 7 days off treatment to comprise a cycle of 28 days, and fulvestrant 500 mg administered intramuscularly on Cycle 1, Days 1 and 15, and then on Day 1 of every 28-day cycle. Patients received treatment until disease progression or unacceptable toxicity. In addition, all pre/perimenopausal women and men received an LHRH agonist throughout therapy.

The baseline demographic and disease characteristics were: median age 54 years (range: 27 to 79 years); 98% female; 38% pre/perimenopausal; 59% White, 38% Asian, 2.5% unknown, 0.6% Black or African American; 6% Hispanic or Latino; and Eastern Cooperative Oncology Group (ECOG) performance status of 0 (63%) or 1 (36%). Tamoxifen (57%) and aromatase inhibitors (50%) were the most commonly used adjuvant endocrine therapies. Sixty-four percent of patients were considered to have secondary endocrine resistance. Eighty-three percent of patients had received prior chemotherapy (in the neo/adjuvant setting) and 1.2% of patients had been treated with a CDK4/6 inhibitor.

The major efficacy outcome measure was investigator (INV)-assessed progression-free survival (PFS) per Response Evaluation Criteria in Solid Tumors (RECIST) version 1.1. Additional efficacy outcome measures included overall survival (OS), INV-assessed objective response rate (ORR), and INV-assessed duration of response (DOR).

Efficacy results are summarized in Table 6 and Figure 1. INV-assessed PFS results were supported by consistent results from a blinded independent central review (BICR) assessment. At the time of the PFS analysis, OS data were not mature with 30% deaths in the overall population.

Table 6: Efficacy Results in Patients with Locally Advanced or Metastatic Breast Cancer in INAVO120
Efficacy Endpoint | ITOVEBI + Palbociclib + Fulvestrant N=161 | Placebo + Palbociclib + Fulvestrant N=164
Progression-Free Survival [Per RECIST version 1.1.] , [Based on investigator assessment.]
Patients with event, n (%) | 82 (51) | 113 (69)
Median, months (95% CI) | 15.0 (11.3, 20.5) | 7.3 (5.6, 9.3)
Hazard ratio (95% CI) | 0.43 (0.32, 0.59)
p-value | < 0.0001
Objective Response Rate,, [Based on confirmed ORR.]
Patients with CR or PR, n (%) | 94 (58) | 41 (25)
95% CI | (50, 66) | (19, 32)
Duration of Response
Median DOR, months (95% CI) | 18.4 (10.4, 22.2) | 9.6 (7.4, 16.6)
CI = confidence interval; CR = complete response; DOR = duration of response; PR = partial response

Figure 1: Kaplan-Meier Curve for Investigator-Assessed Progression-Free Survival in INAVO120

16 HOW SUPPLIED/STORAGE AND HANDLING

ITOVEBI is supplied in the following strengths and package configurations:

Package Configuration | Tablet Strength | NDC | Tablet Description
Bottle of 28 tablets | 3 mg | 50242-084-08 | Red and round convex-shaped with an "INA 3" debossing on one side
Bottle of 28 tablets | 9 mg | 50242-079-08 | Pink and oval-shaped with an "INA 9" debossing on one side

STORAGE AND HANDLING

Store at 20°C to 25°C (68°F to 77°F), excursions permitted between 15°C and 30°C (between 59°F and 86°F) [see USP Controlled Room Temperature]. Store in the original container and keep the bottle tightly closed in order to protect from moisture.

17 PATIENT COUNSELING INFORMATION

Advise the patient to read the FDA-approved patient labeling (Patient Information).

Hyperglycemia

Advise patients that ITOVEBI may cause severe or fatal hyperglycemia, including ketoacidosis, and that monitoring fasting glucose levels before and periodically during therapy is needed. Advise patients to contact their healthcare provider immediately for signs and symptoms of hyperglycemia (e.g., excessive thirst, urinating more often, blurred vision, confusion, difficulty breathing, or increased appetite with weight loss) [see Warnings and Precautions (5.1)].

Stomatitis

Advise patients that ITOVEBI may cause stomatitis, which may be severe, and to notify their healthcare provider if they develop symptoms of stomatitis (e.g., painful redness, swelling, or sores in the mouth) [see Warnings and Precautions (5.2)].

Diarrhea

Advise patients that ITOVEBI may cause diarrhea, which may be severe, and to start anti-diarrheal treatment, increase oral fluids, and notify their healthcare provider if diarrhea occurs while taking ITOVEBI [see Warnings and Precautions (5.3)].

Embryo-Fetal Toxicity

- Inform pregnant women and females of reproductive potential of the potential risk to a fetus. Advise females to inform their healthcare provider of a known or suspected pregnancy [see Warnings and Precautions (5.4) and Use in Specific Populations (8.1)].
- Advise females of reproductive potential to use effective non-hormonal contraception during treatment with ITOVEBI and for 1 week after the last dose [see Use in Specific Populations (8.3)].
- Advise male patients with female partners of reproductive potential to use effective contraception during treatment with ITOVEBI and for 1 week after the last dose [see Use in Specific Populations (8.3)].
- Refer to the Full Prescribing Information of palbociclib and fulvestrant for pregnancy and contraception information.

Lactation

Advise women not to breastfeed during treatment with ITOVEBI and for 1 week after the last dose [see Use in Specific Populations (8.2)]. Refer to the Full Prescribing Information of palbociclib and fulvestrant for lactation information.

Infertility

Advise females and males of reproductive potential that ITOVEBI may impair fertility [see Use in Specific Populations (8.3)]. Refer to the Full Prescribing Information of palbociclib and fulvestrant for infertility information.

Dosing

- Instruct patients to take ITOVEBI at approximately the same time each day [see Dosage and Administration (2.3)].
- Instruct patients that if a dose of ITOVEBI is missed, to take the missed dose as soon as possible within 9 hours. After more than 9 hours, skip the dose and take the next dose at the scheduled time [see Dosage and Administration (2.3)].
- Instruct patients that if vomiting occurs after taking the ITOVEBI dose, do not take an additional dose on that day. Resume the usual dosing schedule the next day [see Dosage and Administration (2.3)].

Distributed by:
Genentech, Inc.
A Member of the Roche Group
1 DNA Way
South San Francisco, CA 94080-4990
ITOVEBI is a registered trademark of Genentech, Inc.
©2025 Genentech, Inc. All rights reserved.

PATIENT INFORMATION
ITOVEBI® (eye-TOVE-bee)
(inavolisib)
tablets, for oral use

Important: ITOVEBI is used with palbociclib and fulvestrant. You should also read the Patient Information that comes with palbociclib and fulvestrant.

What is ITOVEBI?
ITOVEBI is a prescription medicine used in combination with the medicines palbociclib and fulvestrant to treat adults who have hormone receptor (HR)-positive, human epidermal growth factor receptor 2 (HER2)-negative breast cancer that has an abnormal phosphatidylinositol-3-kinase catalytic subunit alpha (PIK3CA) gene, and has spread to nearby tissue or lymph nodes (locally advanced), or to other parts of the body (metastatic), and has come back after hormone (endocrine) therapy.
Your healthcare provider will test your cancer for abnormal PIK3CA genes to make sure that ITOVEBI is right for you.
It is not known if ITOVEBI is safe and effective in children.

Before you take ITOVEBI, tell your healthcare provider about all of your medical conditions, including if you:

- have a history of diabetes or high blood sugar.
- have kidney problems.
- are pregnant or plan to become pregnant. ITOVEBI can harm your unborn baby.
  Females who are able to become pregnant:
  - Your healthcare provider will check to see if you are pregnant before you start treatment with ITOVEBI.
  - You should use effective non-hormonal birth control (contraception) during treatment with ITOVEBI and for 1 week after your last dose. Talk to your healthcare provider about what birth control method is right for you during this time.
  - Tell your healthcare provider right away if you become pregnant or think you may be pregnant during treatment with ITOVEBI.
  Males with female partners who are able to become pregnant:
  - You should use effective birth control (contraception) during treatment with ITOVEBI and for 1 week after your last dose.
- are breastfeeding or plan to breastfeed. It is not known if ITOVEBI passes into your breastmilk. Do not breastfeed during treatment with ITOVEBI and for 1 week after your last dose. Talk to your healthcare provider about the best way to feed your baby during treatment with ITOVEBI.

Tell your healthcare provider about all the medicines you take, including prescription and over-the-counter medicines, vitamins, and herbal supplements.

How should I take ITOVEBI?

- Take ITOVEBI exactly as your healthcare provider tells you to take it.
- Do not change your dose or stop taking ITOVEBI unless your healthcare provider tells you.
- Take ITOVEBI 1 time each day, at about the same time each day.
- Take ITOVEBI with or without food.
- Swallow ITOVEBI tablet(s) whole. Do not chew, crush, or split the tablet(s).
- If you miss a dose of ITOVEBI, you may still take your missed dose within 9 hours from the time you usually take it. If it has been more than 9 hours after you usually take your dose, skip the dose for that day. The next day, take the dose at your usual time.
- If you vomit after taking a dose of ITOVEBI, do not take an extra dose on that day. Take your regular dose of ITOVEBI at your usual time the next day.
- For women who have not reached menopause or are just starting menopause, your healthcare provider will prescribe a medicine called luteinizing hormone-releasing hormone (LHRH) agonist. For men, your healthcare provider may prescribe a LHRH agonist.

What are the possible side effects of ITOVEBI?
ITOVEBI may cause serious side effects, including:

- High blood sugar levels (hyperglycemia). High blood sugar is common with ITOVEBI, and may be severe or fatal. Untreated severe hyperglycemia can lead to a condition called diabetic ketoacidosis that can happen in people treated with ITOVEBI. Diabetic ketoacidosis is a serious condition that requires treatment in a hospital and that can lead to death. Your healthcare provider will monitor your blood sugar levels before you start and during treatment with ITOVEBI. Your blood sugar levels may be monitored more often if you have a history of Type 2 diabetes. Your healthcare provider may also ask you to self-monitor and report your blood sugar levels at home. This will be required more frequently in the first 4 weeks of treatment. If you are not sure how to test your blood sugar levels, talk to your healthcare provider. You should stay well-hydrated during treatment with ITOVEBI.
  Tell your healthcare provider right away if you develop symptoms of high blood sugar, including:

- difficulty breathing
- nausea and vomiting (lasting more than 2 hours)
- stomach pain
- excessive thirst
- dry mouth
- more frequent urination than usual or a higher amount of urine than normal

- blurred vision
- unusually increased appetite
- weight loss
- fruity-smelling breath
- flushed face and dry skin
- feeling unusually sleepy or tired
- confusion

- Mouth sores (stomatitis). Mouth sores are common with ITOVEBI and may be severe. Tell your healthcare provider if you develop any of the following in your mouth:

- pain
- redness

- swelling
- ulcers

- Diarrhea. Diarrhea is common with ITOVEBI and may be severe. Severe diarrhea can lead to the loss of too much body water (dehydration) and kidney injury. Tell your healthcare provider right away if you develop diarrhea, stomach-area (abdominal) pain, or see mucus or blood in your stool during treatment with ITOVEBI. Your healthcare provider may tell you to drink more fluids or take medicines to treat your diarrhea.

Your healthcare provider may tell you to decrease your dose, temporarily stop your treatment, or completely stop your treatment with ITOVEBI if you develop certain serious side effects.
The most common side effects and abnormal blood test results of ITOVEBI when used in combination with palbociclib and fulvestrant include:

- decreased white blood cell counts, red blood cell counts, and platelet counts
- decreased blood levels of calcium, potassium, sodium, and magnesium
- increased creatinine blood levels
- tiredness

- increased blood levels of the liver enzyme alanine transaminase (ALT)
- nausea
- rash
- loss of appetite
- COVID-19 infection
- headache

ITOVEBI may affect fertility in males and in females who are able to become pregnant. Talk to your healthcare provider if this is a concern for you.
These are not all of the possible side effects of ITOVEBI.
Call your healthcare provider for medical advice about side effects. You may report side effects to FDA at 1-800-FDA-1088.

How should I store ITOVEBI?

- Store ITOVEBI at room temperature between 68°F to 77°F (20°C to 25°C).
- Store ITOVEBI in the original container and keep the bottle tightly closed to protect from moisture.

Keep ITOVEBI and all medicines out of the reach of children.

General information about the safe and effective use of ITOVEBI.
Medicines are sometimes prescribed for purposes other than those listed in a Patient Information leaflet. Do not use ITOVEBI for a condition for which it was not prescribed. Do not give ITOVEBI to other people, even if they have the same symptoms that you have. It may harm them. You can ask your pharmacist or healthcare provider for information about ITOVEBI that is written for health professionals.

What are the ingredients in ITOVEBI?
Active ingredient: inavolisib
Inactive ingredients: lactose, magnesium stearate, microcrystalline cellulose, and sodium starch glycolate. The tablet film-coating contains iron oxide red, and iron oxide yellow (in the 9 mg tablet only), macrogol/polyethylene glycol, polyvinyl alcohol (partially hydrolyzed), talc, and titanium dioxide.
Distributed by: Genentech, Inc., A Member of the Roche Group, 1 DNA Way, South San Francisco, CA 94080-4990
ITOVEBI is a registered trademark of Genentech, Inc.
For more information, go to www.ITOVEBI.com or call 1-877-436-3683.

This Patient Information has been approved by the U.S. Food and Drug Administration.

Revised: 12/2025

PRINCIPAL DISPLAY PANEL - 9 mg Tablet Bottle Carton

NDC 50242-079-08

Itovebi®
(inavolisib)
Tablets

9 mg

Swallow tablets whole.

DO NOT chew, crush,
or split tablets.

28 Tablets

Rx only
Genentech

11039960

PRINCIPAL DISPLAY PANEL - 3 mg Tablet Bottle Carton

NDC 50242-084-08

Itovebi®
(inavolisib)
Tablets

3 mg

Swallow tablets whole.

DO NOT chew, crush,
or split tablets.

28 Tablets

Rx only
Genentech

11039843